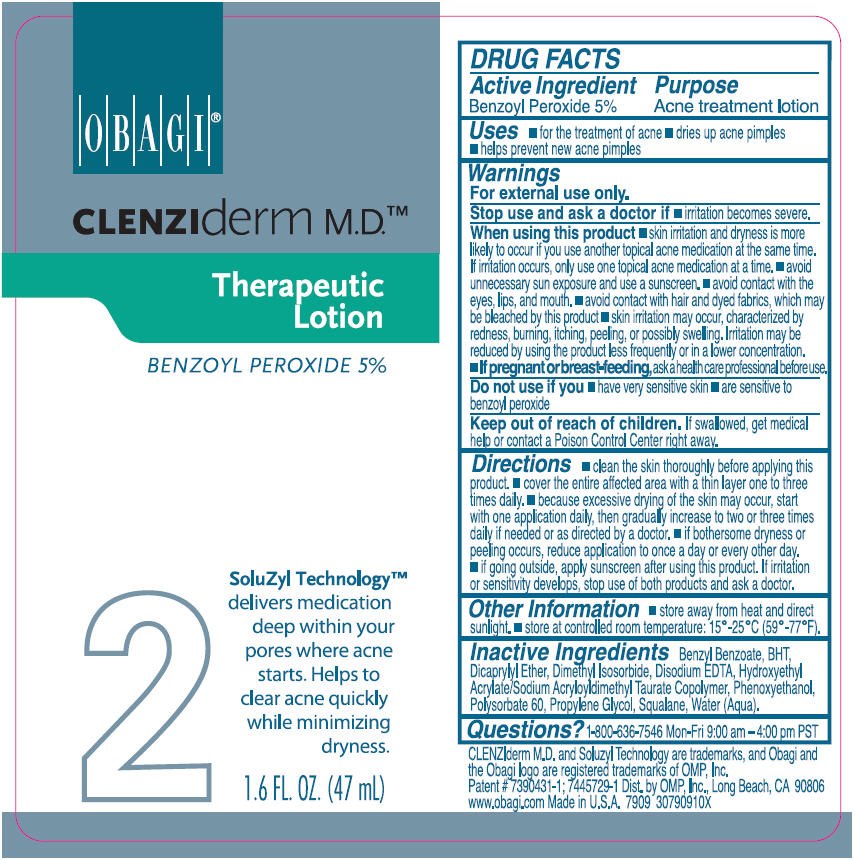 DRUG LABEL: CLENZIDERM THERAPEUTIC
NDC: 62032-113 | Form: LOTION
Manufacturer: OMP, INC.
Category: otc | Type: HUMAN OTC DRUG LABEL
Date: 20120103

ACTIVE INGREDIENTS: BENZOYL PEROXIDE 50 mg/1 mL
INACTIVE INGREDIENTS: BENZYL BENZOATE; DICAPRYLYL ETHER; PROPYLENE GLYCOL; SQUALANE; POLYSORBATE 60; DIMETHYL ISOSORBIDE; PHENOXYETHANOL; EDETATE DISODIUM; BUTYLATED HYDROXYTOLUENE; WATER

OBAGI®
CLENZIderm M.D.™
Therapeutic Lotion

DRUG FACTS

Active Ingredient

Benzoyl Peroxide 5%

Purpose

Acne treatment lotion

Uses

- for the treatment of acne
- dries up acne pimples
- helps prevent new acne pimples

Warnings

For external use only.

Stop use and ask a doctor if

- irritation becomes severe.

When using this product

- skin irritation and dryness is more likely to occur if you use another topical acne medication at the same time. If irritation occurs, only use one topical acne medication at a time.
- avoid unnecessary sun exposure and use a sunscreen.
- avoid contact with the eyes, lips and mouth.
- avoid contact with hair and dyed fabrics, which may be bleached by this product
- skin irritation may occur, characterized by redness, burning, itching, peeling, or possibly swelling. Irritation may be reduced by using the product less frequently or in a lower concentration.

PREGNANCY OR BREAST FEEDING

- If pregnant or breast-feeding, ask a health care professional before use.

Do not use if you

- have very sensitive skin
- are sensitive to benzoyl peroxide

Keep out of reach of children

If swallowed, get medical help or contact a Poison Control Center right away.

Directions

- clean the skin thoroughly before applying this product.
- cover the entire affected area with a thin layer one to three times daily.
- because excessive drying of the skin may occur, start with one application daily, then gradually increase to two or three times daily if needed or as directed by a doctor.
- if bothersome dryness or peeling occurs, reduce application to once a day or every other day.
- if going outside, apply sunscreen after using this product. If irritation or sensitivity develops, stop use of both products and ask a doctor.

Other Information

- store away from heat and direct sunlight.
- store at controlled room temperature: 15°-25°C (59°-77°F).

Inactive Ingredients

Benzyl Benzoate, BHT, Dicaprylyl Ether, Dimethyl Isosorbide, Disodium EDTA, Hydroxyethyl Acrylate/Sodium Acryloyldimethyl Taurate Copolymer, Phenoxyethanol, Polysorbate 60, Propylene Glycol, Squalane, Water (Aqua).

Questions?

1-800-636-7546 Mon-Fri 9:00 am – 4:00 pm PST

Dist. by OMP, Inc., Long Beach, CA 90806

PRINCIPAL DISPLAY PANEL - 47 mL Bottle Label

OBAGI®

CLENZIderm M.D.™

Therapeutic
Lotion

BENZOYL PEROXIDE 5%

2
SoluZyl Technology™
delivers medication
deep within your
pores where acne
starts. Helps to
clear acne quickly
while minimizing
dryness.

1.6 FL. OZ. (47 mL)